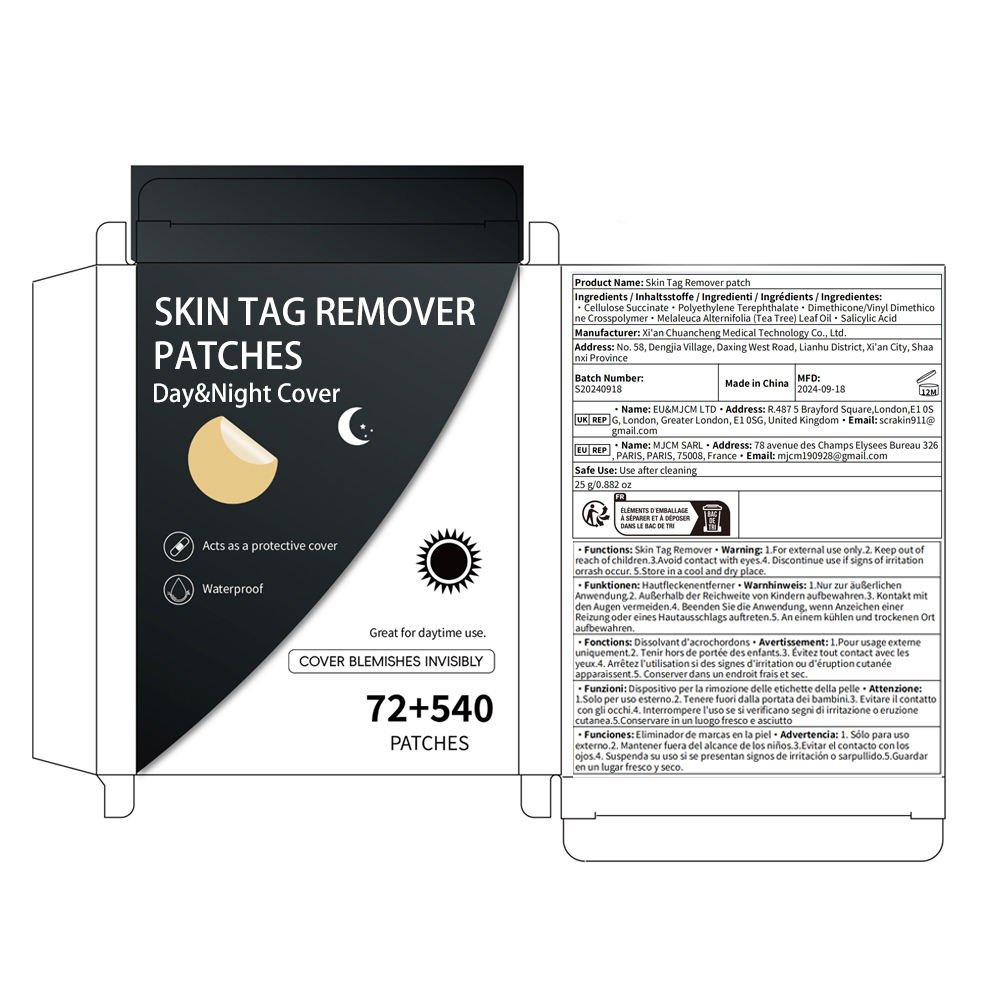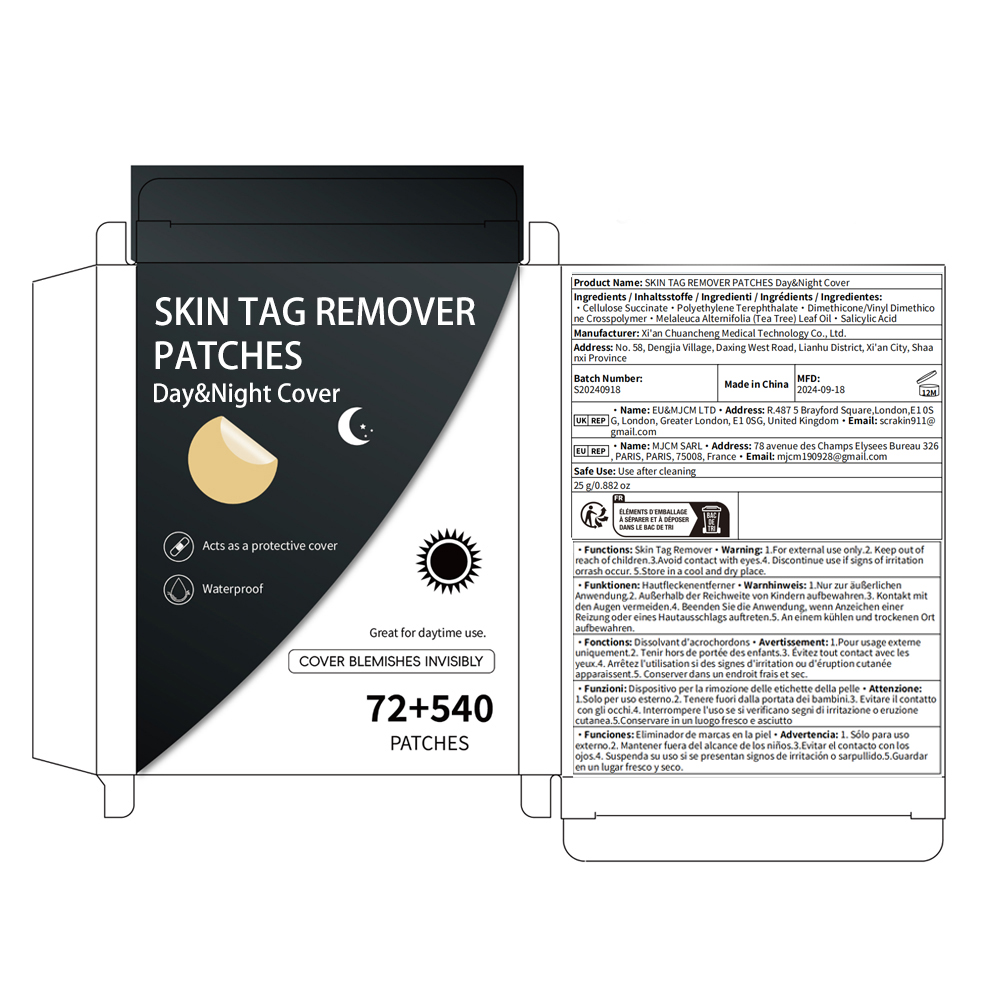 DRUG LABEL: Skin Tag Remover patch
NDC: 84758-001 | Form: PATCH
Manufacturer: Xi'an Chuancheng Medical Technology Co., Ltd.
Category: otc | Type: HUMAN OTC DRUG LABEL
Date: 20240919

ACTIVE INGREDIENTS: SALICYLIC ACID 0.5 g/100 g; MELALEUCA ALTERNIFOLIA (TEA TREE) LEAF OIL 0.5 g/100 g
INACTIVE INGREDIENTS: CELLULOSE SULFATE 47.5 g/100 g; POLYETHYLENE TEREPHTHALATE (INTRINSIC VISCOSITY 0.40-0.70) 35 g/100 g; DIMETHICONE/VINYL DIMETHICONE CROSSPOLYMER (HARD PARTICLE) 16.5 g/100 g

ACTIVE INGREDIENT

Melaleuca Alternifolia (Tea Tree) Leaf Oil 0.5%
Salicylic Acid 0.5%

PURPOSE

skin tag remover

INDICATIONS AND USAGE

1. Prep your skin. Cleanse and dry pimple area.
2.Patch the tag. Leave on for 6-8 hours.
3.Watch it work. Peel off when patch turns white.

WARNINGS

For external use only.

STORAGE AND HANDLING

Stop using and ask a doctor if a rash and/or irritationoccurs.

DO NOT USE

on damaged or broken skin

WHEN USING

keep out of eyes. Rinse with water to remove.

KEEP OUT OF REACH OF CHILDREN

If swallowed, get medical help or contact a Poison Control Center right away.